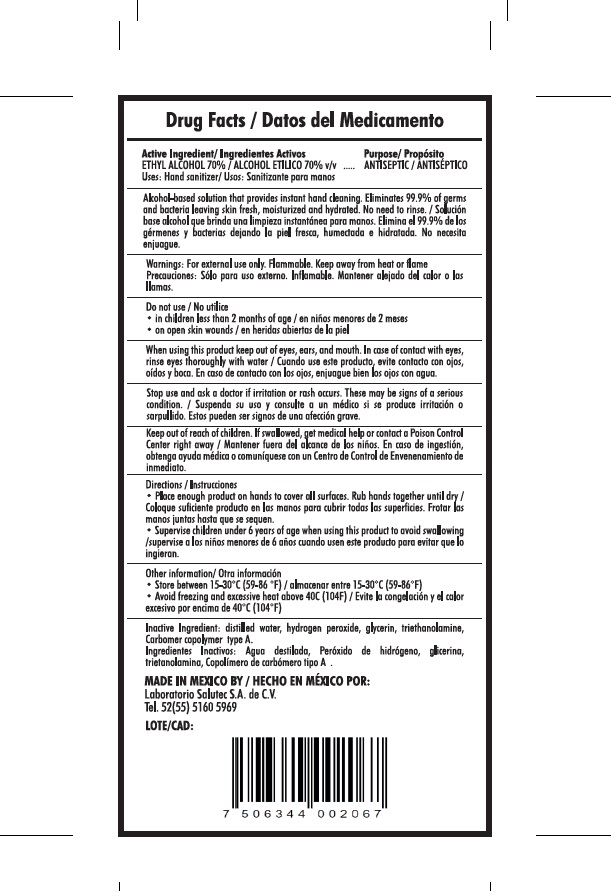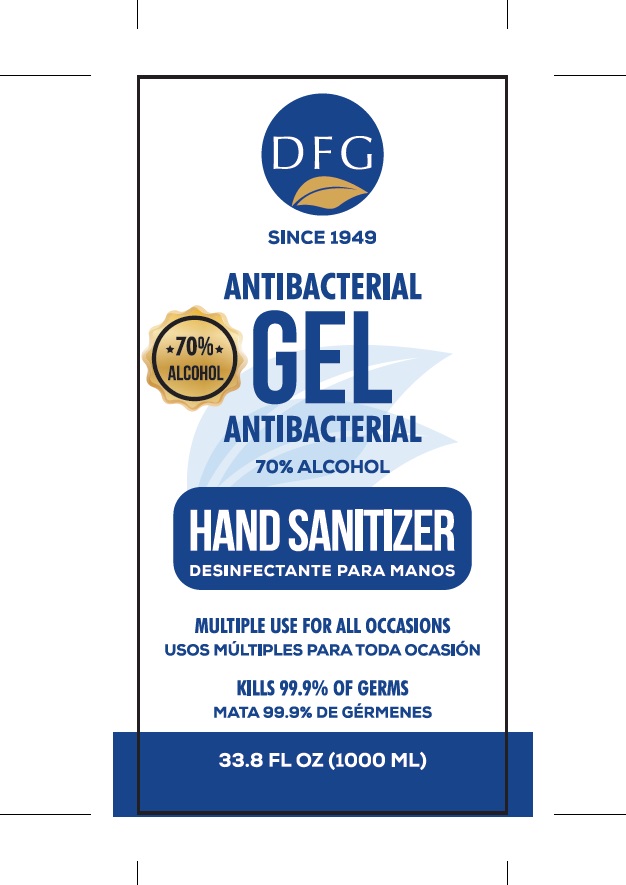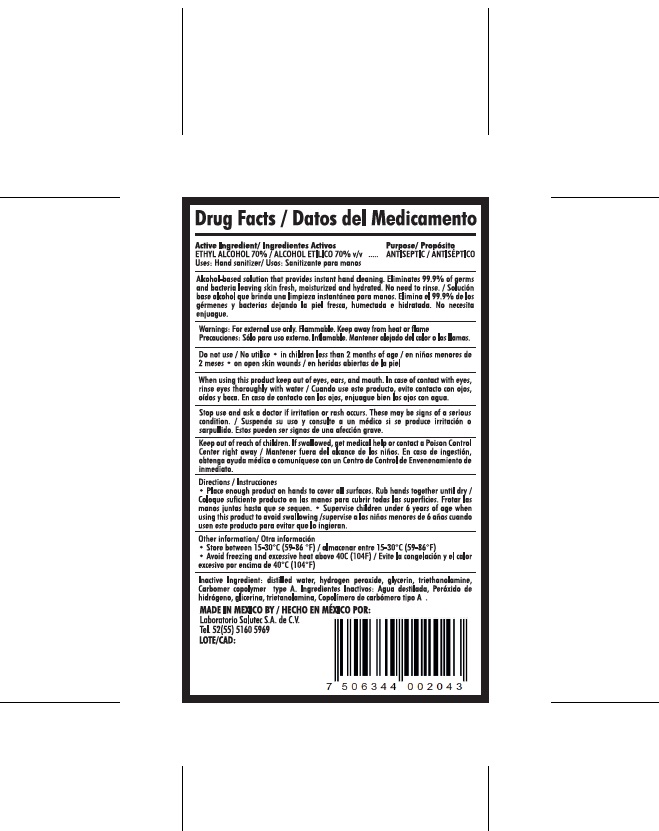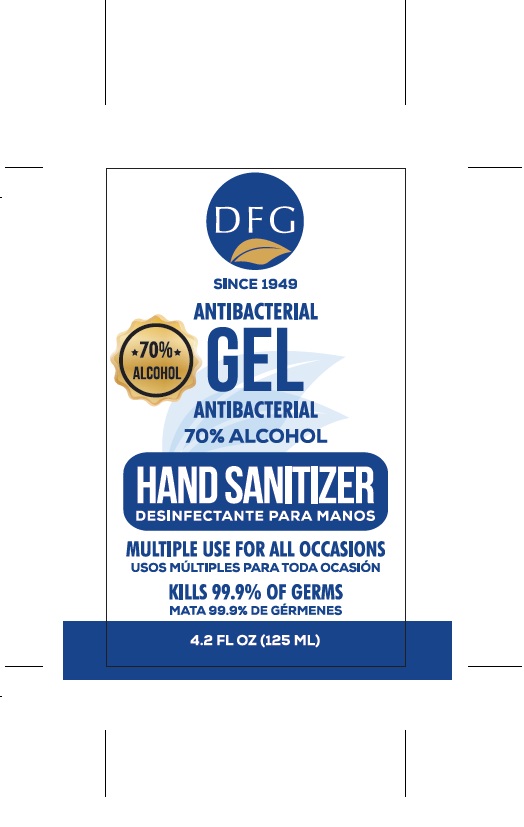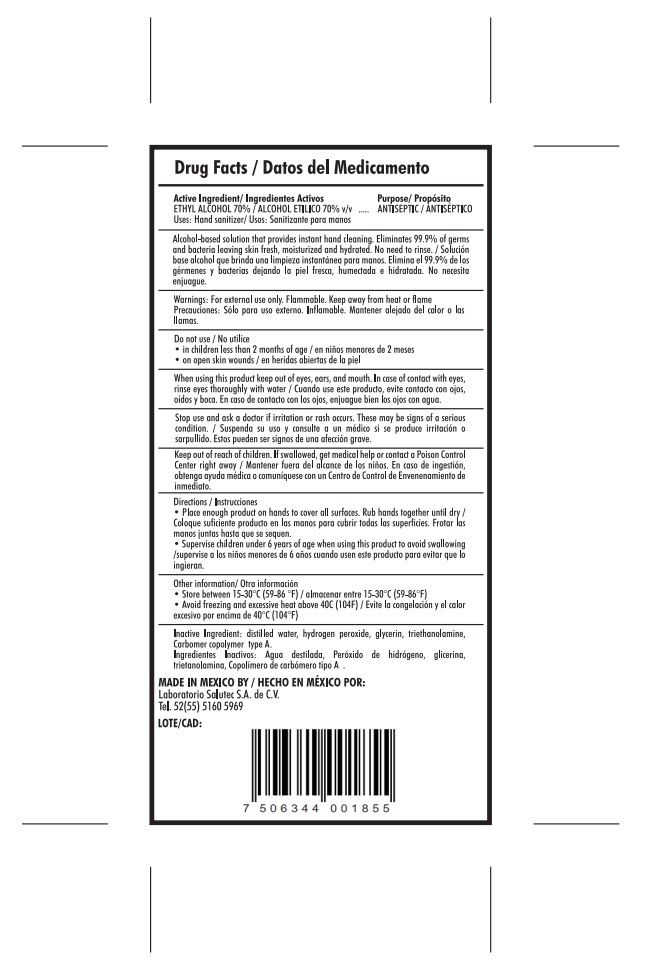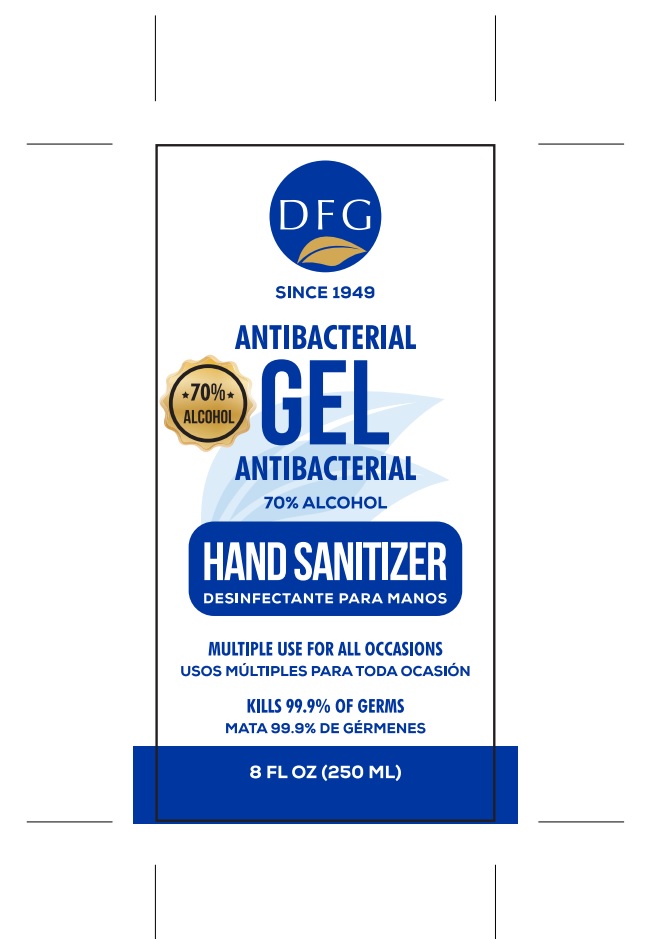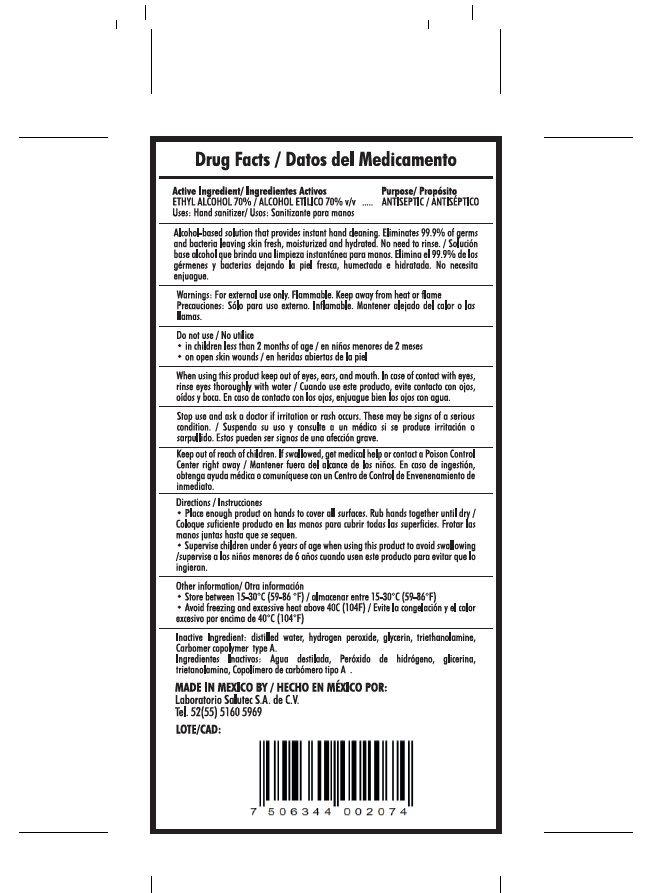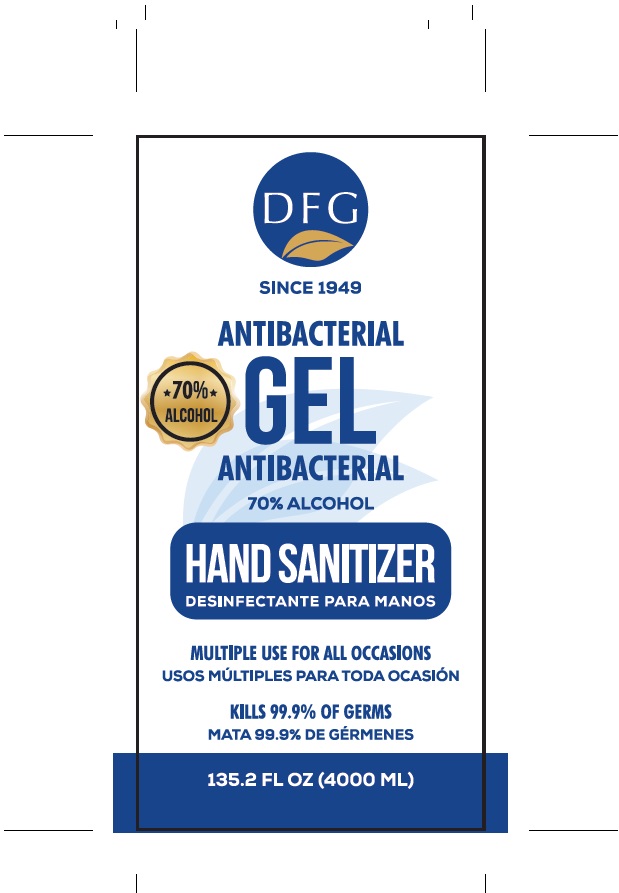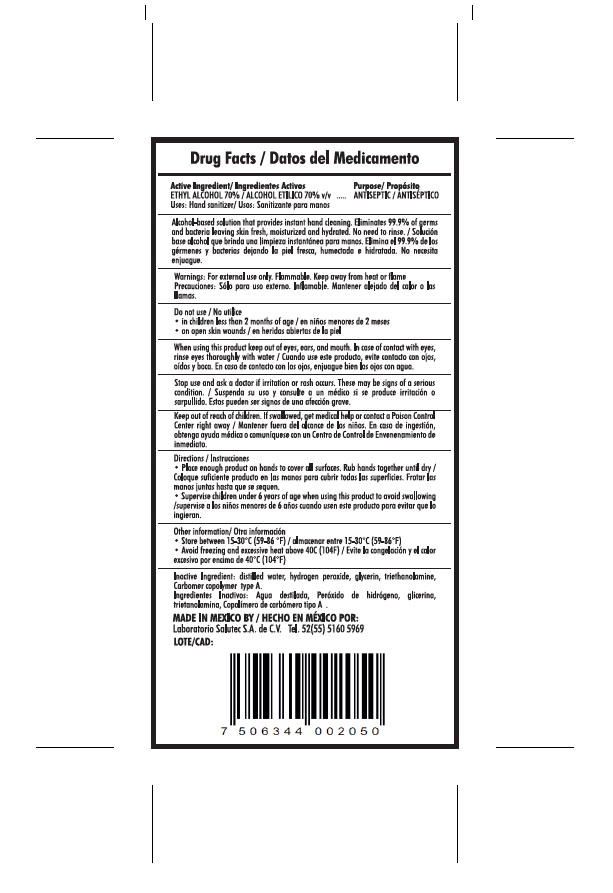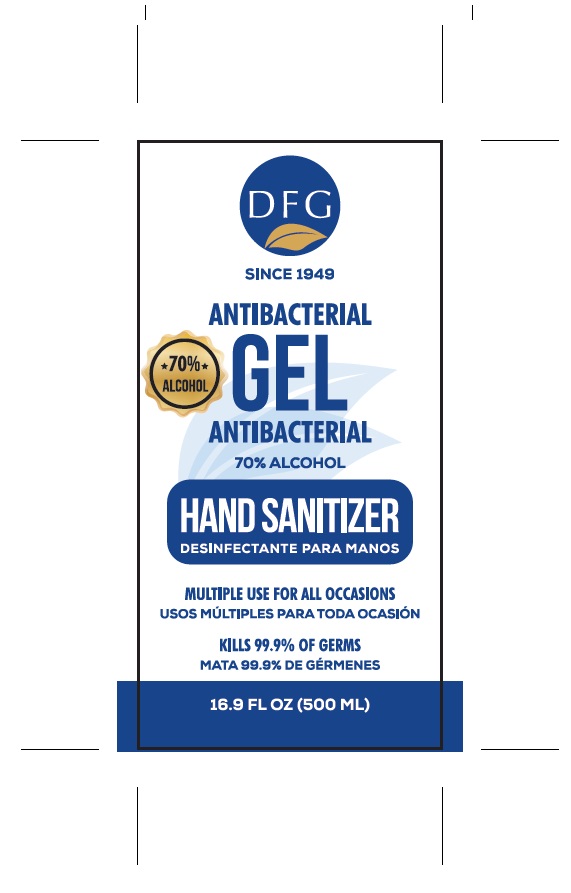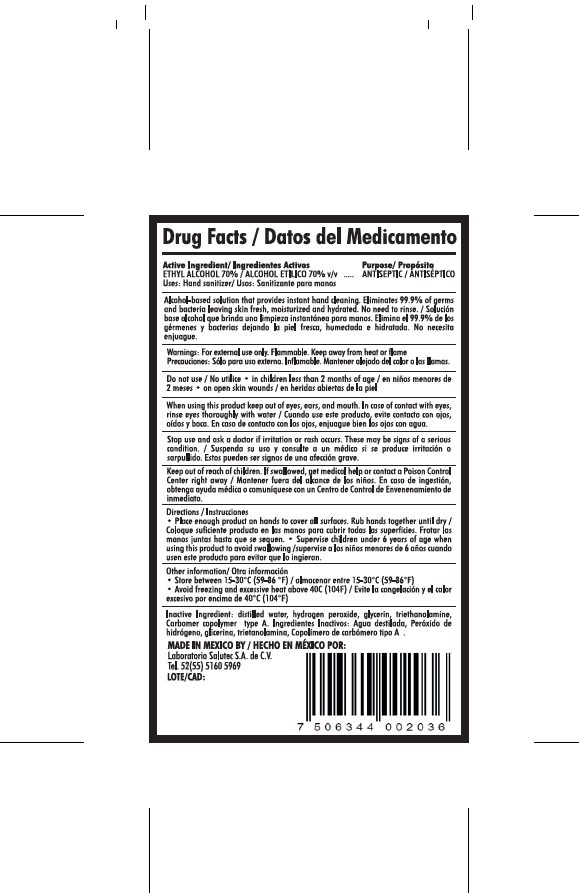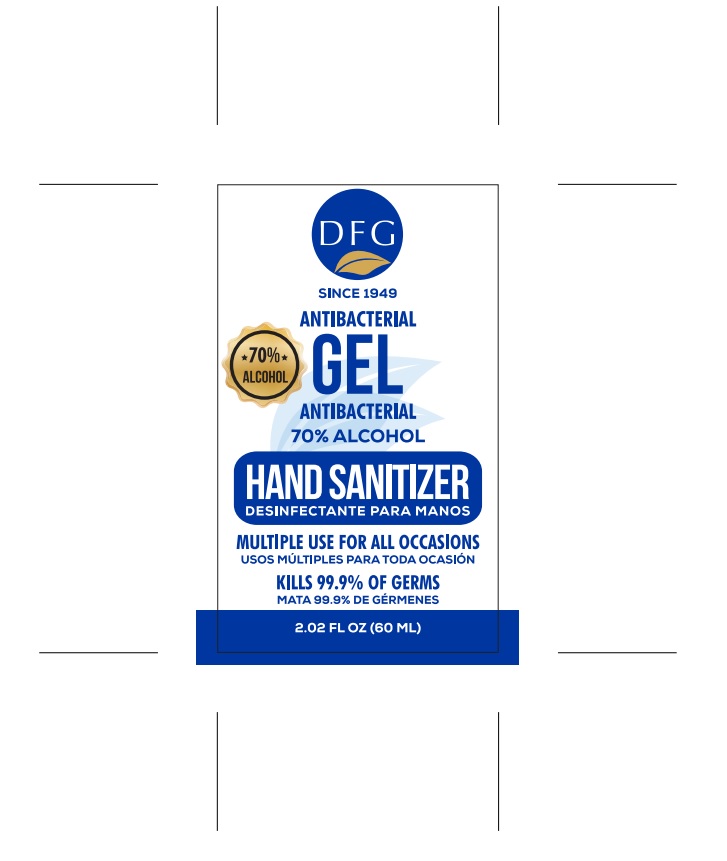 DRUG LABEL: Hand Sanitizer
NDC: 79289-001 | Form: GEL
Manufacturer: Laboratorio Salutec, S.A. de C.V.
Category: otc | Type: HUMAN OTC DRUG LABEL
Date: 20200727

ACTIVE INGREDIENTS: ALCOHOL 73 mL/100 mL
INACTIVE INGREDIENTS: HYDROGEN PEROXIDE 0.125 mL/100 mL; TROLAMINE 1 g/100 mL; CARBOMER COPOLYMER TYPE A 7 g/100 mL; GLYCERIN 1 g/100 mL; WATER 17.875 mL/100 mL

This is a gel hand sanitizer

The gel hand sanitizer is manufactured using only the following ingredients consistent with World Health Organization (WHO) recommendations:

1. Alcohol (ethanol) (USP or Food Chemical Codex (FCC) grade) (70%, volume/volume (v/v)) in an aqueous solution denatured according to Alcohol and Tobacco Tax and Trade Bureau regulations in 27 CFR part 20.
2. Glycerol (1% v/v).
3. Sterile distilled water or boiled cold water.
  d. Carbomer
  e. Trolamine

The firm does not add other active or inactive ingredients. Different or additional ingredients may impact the quality and potency of the product.

Active Ingredient(s)

Alcohol 70% v/v. Purpose: Antiseptic

Purpose

Antiseptic, Gel Hand Sanitizer

Use

Gel Hand Sanitizer to help reduce bacteria that potentially can cause disease. For use when soap and water are not available.

Warnings

For external use only. Flammable. Keep away from heat or flame

Do not use

- in children less than 2 months of age
- on open skin wounds

When using this product keep out of eyes, ears, and mouth. In case of contact with eyes, rinse eyes thoroughly with water.
Stop use and ask a doctor if irritation or rash occurs. These may be signs of a serious condition.
Keep out of reach of children. If swallowed, get medical help or contact a Poison Control Center right away.

Stop use and ask a doctor if irritation or rash occurs. These may be signs of a serious condition.

Keep out of reach of children. If swallowed, get medical help or contact a Poison Control Center right away.

Directions

- Place enough product on hands to cover all surfaces. Rub hands together until dry.
- Supervise children under 6 years of age when using this product to avoid swallowing.

Other information

- Store between 15-30C (59-86F)
- Avoid freezing and excessive heat above 40C (104F)

Inactive ingredients

Carbomer, Water, Trolamine, Glycerin

Package Label - Principal Display Panel

250 mL NDC: 79289-001-01

500 mL NDC: 79289-001-05
4000 mL NDC: 79289-001-04
125 mL NDC: 79289-001-03
1000 mL NDC: 79289-001-02
60 mL NDC: 79289-001-06